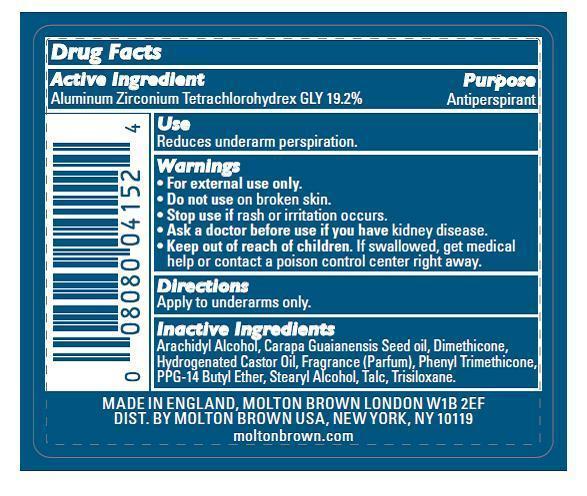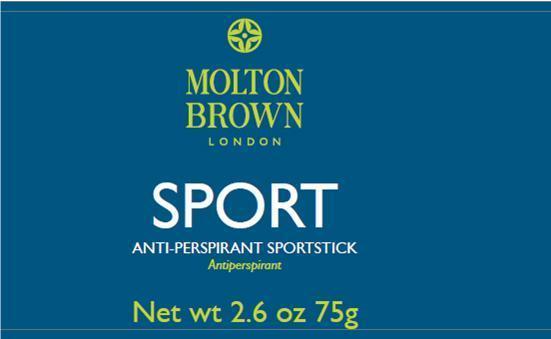 DRUG LABEL: Sport Anti-Perpirant Sportstick
NDC: 68814-145 | Form: STICK
Manufacturer: Molton Brown LTD (UK)
Category: otc | Type: HUMAN OTC DRUG LABEL
Date: 20150511

ACTIVE INGREDIENTS: ALUMINUM ZIRCONIUM OCTACHLOROHYDREX GLY 14.4 g/75 g
INACTIVE INGREDIENTS: ARACHIDYL ALCOHOL; CARAPA GUIANENSIS SEED OIL; DIMETHICONE; HYDROGENATED CASTOR OIL; PHENYL TRIMETHICONE; PPG-14 BUTYL ETHER; STEARYL ALCOHOL; TALC; TRISILOXANE

Sport Anti-Perspirant Sportstick

Active Ingredient.................... Purpose

Aluminum Zirconium Tetra Cholorhydrex GLY............ Antiperspirant

keep out of reach of children. If swallowed, get medical help or contact a poison control center right away.

For external use only

Do not use on broken skin

Ask a doctor before use if you have kidney disease

Directions

Apply to the underarms only.

Inactive Ingredients

Arachidyl Alcohol, Carapa Guaianensis Seed Oil, Dimethicone, Hydrogenated Castor Oil, Fragrance (Parfum), Phenyl Trimethicone, PPG-14 Butyl Ether, Stearyl Alcohol, Talc, Trisiloxane.

PACKAGE LABEL

Molton Brown London

Sport Anti-Perspirant Sportstick

Antiperspirant

Net wt. 2.6 oz 75g